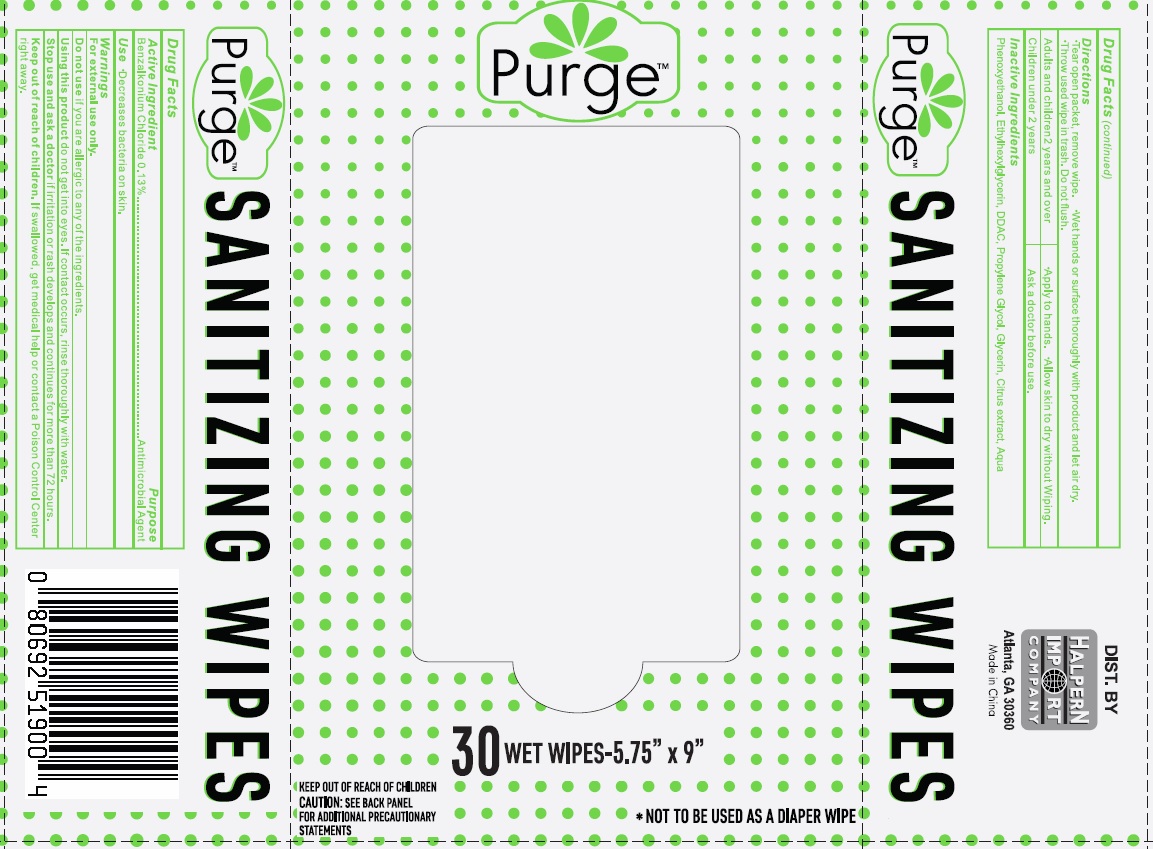 DRUG LABEL: Sanitizing Wipes
NDC: 78562-013 | Form: CLOTH
Manufacturer: Halpern Import Company
Category: otc | Type: HUMAN OTC DRUG LABEL
Date: 20200812

ACTIVE INGREDIENTS: BENZALKONIUM CHLORIDE 0.13 1/1 1
INACTIVE INGREDIENTS: PHENOXYETHANOL; ETHYLHEXYLGLYCERIN; PROPYLENE GLYCOL; GLYCERIN; WATER

Active Ingredient

Benalkonium chloride 0.13%

Purpose

Antimicrobial Agent

Use

Decreases bacteria on skin

Warnings

For external use only

Do not use

if you are allegic to any of the ingredients.

Using this product

do not get into eyes. In contact occurs, rinse thoroughly with water.

Stop use and ask a doctor

if irritation or rash develops and continues for more than 72 hours

Keep out of reach of children.

If swallowed, get medical help or contact a Poison Control Center right away

Directions

- Tear open packet, remove wipe.
- Wet hands or surface thoroughly with product and let air dry.
- Throw used wipe in trash. Do not flush.

Inactive Ingredients

Phenoxyethanol, Ethylhexylglycerin, DDAC, Propylene Glycol, Glycerin, Citrus extract, Aqua

Principal Display Panel

NDC 78562-013-30

PurgeTM

SANITIZING WIPES

KEEP OUT OF REACH OF CHILDREN

CAUTION: SEE BACK PANEL FOR ADDITIONAL PRECAUTIONARY STATEMENTS

*NOT TO BE USED AS A DIAPER WIPE

30 WET WIPES - 5.75'' X 9 ''